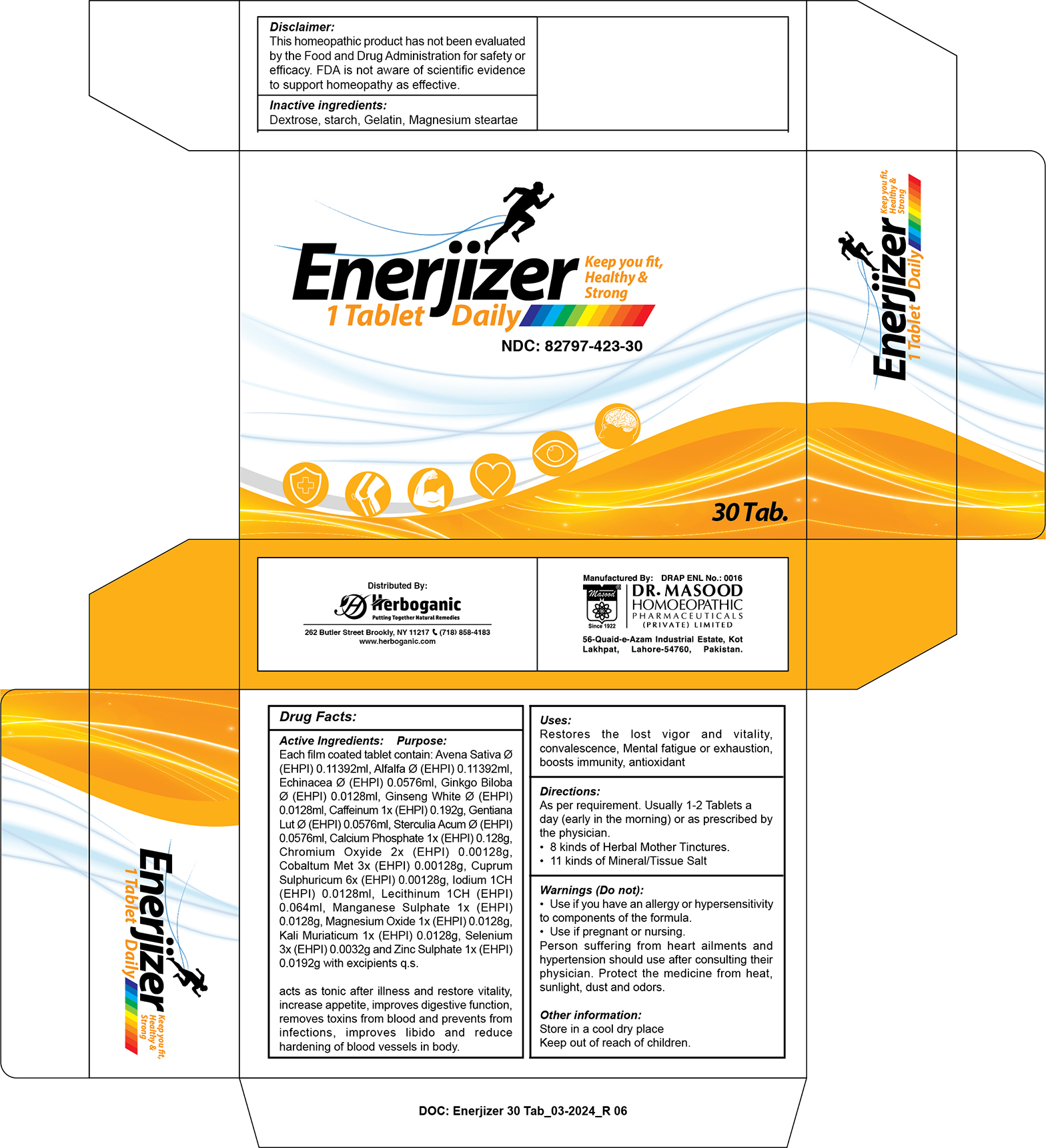 DRUG LABEL: Enerjizer
NDC: 82797-423 | Form: TABLET, COATED
Manufacturer: Dr. Masood Homeopathic Pharmaceuticals Private Limited
Category: homeopathic | Type: HUMAN OTC DRUG LABEL
Date: 20240712

ACTIVE INGREDIENTS: ECHINACEA, UNSPECIFIED 0.0576 mg/660 mg; CHROMIC OXIDE 0.00128 mg/660 mg; AVENA SATIVA WHOLE 0.11392 mg/660 mg; ALFALFA 0.11392 mg/660 mg; CAFFEINE 0.192 mg/660 mg; COBALT 0.00128 mg/660 mg; MAGNESIUM OXIDE 0.0128 mg/660 mg; ZINC SULFATE 0.0192 mg/660 mg; GINKGO BILOBA WHOLE 0.0128 mg/660 mg; GENTIANA LUTEA WHOLE 0.0576 mg/660 mg; CALCIUM PHOSPHATE 0.128 mg/660 mg; BASIC COPPER SULFATE 0.00128 mg/660 mg; PANAX GINSENG WHOLE 0.0128 mg/660 mg; MANGANESE SULFATE 0.0128 mg/660 mg; POTASSIUM CHLORIDE 0.0128 mg/660 mg; COLA ACUMINATA WHOLE 0.0576 mg/660 mg; LECITHIN, SOYBEAN 0.064 mg/660 mg; IODINE 0.0128 mg/660 mg; SELENIUM 0.0032 mg/660 mg
INACTIVE INGREDIENTS: DEXTROSE 247 mg/660 mg; MAGNESIUM STEARATE 7 mg/660 mg; STARCH, CORN 7 mg/660 mg; GELATIN 7 mg/660 mg

Dosage and Administration

As per requirement. Usually 1-2 tablets a day (early in the morning) or as prescribed by licensed practitioner

Indications and Usage

Restores the lost vigour and vitality.

Bad effects of prolonged illness.

Mental fatigue or exhaustion.

Acts as prophylactic against viral diseases.

Lowers cholesterol and control glucose level in body.

Reduce inflammation in body.

Helpful in regulation of blood pressure and reduce fatigue.

Keeps you energetic during exercise.

Makes muscles stronger.

Fulfill iodine deficiency and helpful in thyroid gland functioning.

Prevents from cerebral thrombosis and stroke

Inactive Ingredients

Dextrose

Starch

Gelatin

Magnesium stearate

Active Ingredients

Avena sativa

Alfalfa

Echinacea

Ginkgo biloba

Ginseng

Gentiana

Sterculia acum

Caffeine

Calcium phos

Chromium oxide

Cobaltum met

Cuprum sulf

Iodine

Lecithin

Magnesium

Manganese

Potassium

Selenium

Zincum sulph

Keep out of the reach of children

Keep this and all other medicines out of the reach of children

Purpose

- Avena sativa: acts as tonic after illness and restore vitality.
- Alfalfa: increase appetite, improves digestive function.
- Echinacea: removes toxins from blood and prevents from infections.
- Ginkgo biloba: improves libido and reduce hardening of blood vessels in body.
- Ginseng: beneficial in sciatica, backache, gout pain. Restores body’s vitality after illness.
- Gentiana: improves appetite and acts as a tonic.
- Sterculia acum: maintains blood circulation in body and reduce feeling of fatigue and tiredness.
- Calcium phos: makes bones and teeth stronger.
- Chromium oxide: helpful in backache, shoulders pain, restlessness and laziness.
- Cobaltum met: effective in bone pains, tiredness and sexual weakness.
- Cuprum sulf: essential element for carbohydrates metabolism
- Iodine: accelerate metabolism and essential for the production of thyroid hormones.
- Lecithin: increase RBCs production and increase Hb level.
- Magnesium: helps to maintain normal nerve and muscle function, supports a healthy immune system, and helps bones remain strong.
- Potassium: helpful to reduce blood pressure and water retention, protect against stroke and help prevent osteoporosis and kidney stones.
- Selenium: acts on genitourinary system and affective for sexual weakness in old age.
- Zincum sulph: It is needed for the body's defensive (immune) system to properly

Warnings

Do not:

- use if you have an allergy or hypersensitivity to components of the formula
- use if pregnant or nursing

Person suffering from heart ailments and hypertension should use after consulting their physician.

Protect the medicine from heat, sunlight, dust and odors, keep out of the reach of children.